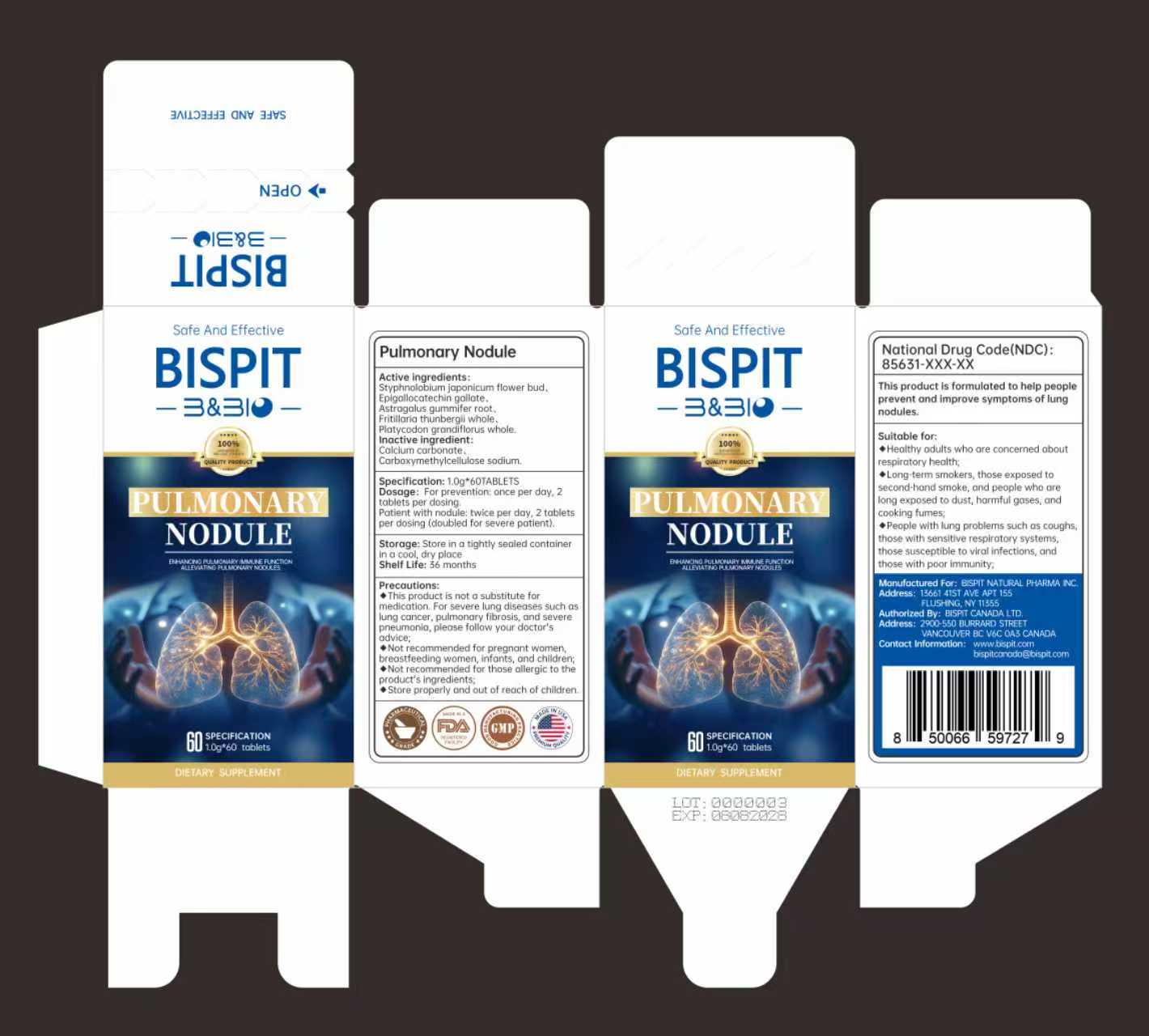 DRUG LABEL: Pulmonary Nodule
NDC: 85631-011 | Form: CAPSULE
Manufacturer: Bispit Canada Ltd.
Category: homeopathic | Type: HUMAN OTC DRUG LABEL
Date: 20251103

ACTIVE INGREDIENTS: EPIGALLOCATECHIN GALLATE 146 mg/1 g; PLATYCODON GRANDIFLORUS WHOLE 73 mg/1 g; ASTRAGALUS GUMMIFER ROOT 122 mg/1 g; STYPHNOLOBIUM JAPONICUM FLOWER BUD 462 mg/1 g; FRITILLARIA THUNBERGII WHOLE 97 mg/1 g
INACTIVE INGREDIENTS: CARBOXYMETHYLCELLULOSE SODIUM; CALCIUM CARBONATE

ACTIVE INGREDIENT

STYPHNOLOBIUM JAPONICUM FLOWER BUD
EPIGALLOCATECHIN GALLATE
ASTRAGALUS GUMMIFER ROOT
FRITILLARIA THUNBERGII WHOLE
PLATYCODON GRANDIFLORUS WHOLE

Store properly and out of reach of children.

PURPOSE

This product is formulated to help peopleprevent and improve symptoms of lungnodules.

INDICATIONS AND USAGE

Suitable for:◆Healthy adults who are concerned aboutrespiratory health;◆Long-term smokers, those exposed tosecond-hand smoke, and people who arelong exposed to dust, harmful gases, andcooking fumes;People with lung problems such as coughsthose with sensitive respiratory systemsthose susceptible to viral infections, andthose with poor immunity

INACTIVE INGREDIENT

CALCIUM CARBONATE
CARBOXYMETHYLCELLULOSE SODIUM

WARNINGS

This product is not a substitute formedication.For severe lung diseases such aslung cancer, pulmonary fibrosis, and severepneumonia, please follow your doctor'sadvice:Not recommended for pregnant women,breastfeeding women, infants, and children;Not recommended for those allergic to theproduct's ingredients;

DOSAGE AND ADMINISTRATION

Dosage: For prevention: once per day,2tablets per dosing.Patient with nodule: twice per day, 2 tabletsper dosing (doubled for severe patient).